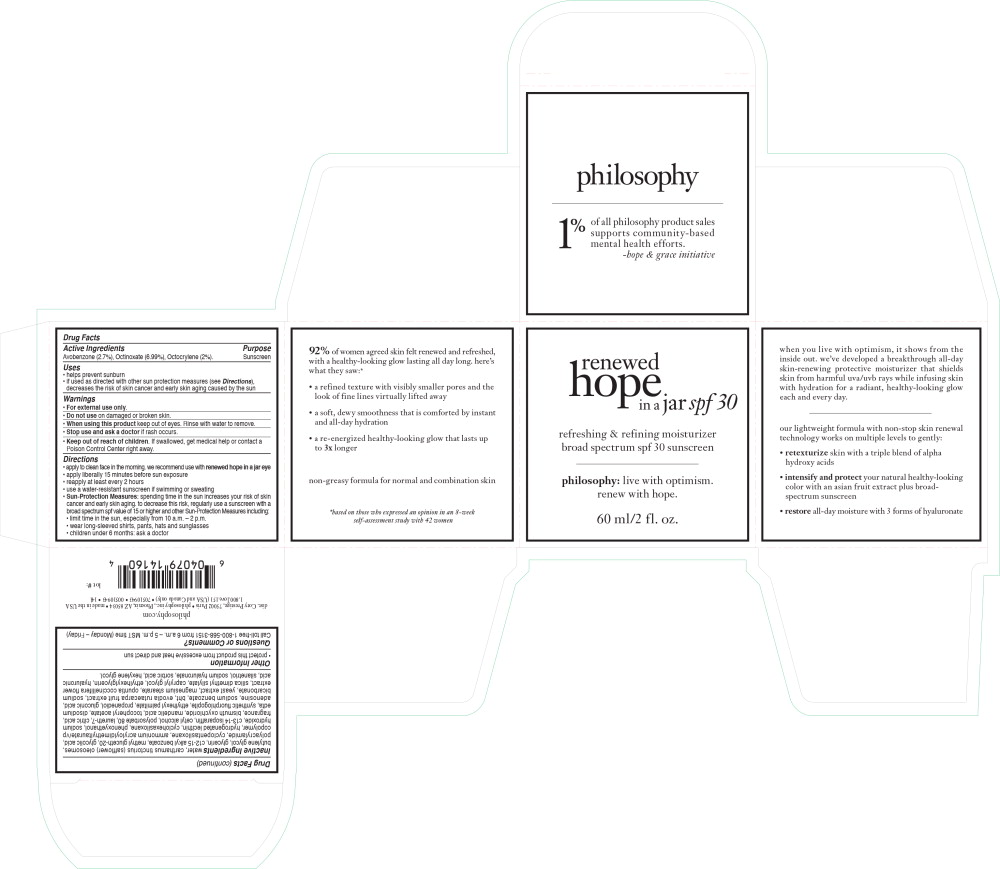 DRUG LABEL: renewed hope in a jar spf 30
NDC: 50184-1011 | Form: CREAM
Manufacturer: Philosophy, Inc.
Category: otc | Type: HUMAN OTC DRUG LABEL
Date: 20230128

ACTIVE INGREDIENTS: AVOBENZONE 2.7 g/100 mL; OCTINOXATE 6.99 g/100 mL; OCTOCRYLENE 2 g/100 mL
INACTIVE INGREDIENTS: WATER; CARTHAMUS TINCTORIUS SEED OLEOSOMES; BUTYLENE GLYCOL; GLYCERIN; ALKYL (C12-15) BENZOATE; METHYL GLUCETH-20; GLYCOLIC ACID; POLYACRYLAMIDE (10000 MW); CYCLOMETHICONE 5; HYDROGENATED SOYBEAN LECITHIN; CYCLOMETHICONE 6; PHENOXYETHANOL; SODIUM HYDROXIDE; C13-14 ISOPARAFFIN; CETYL ALCOHOL; POLYSORBATE 80; LAURETH-7; CITRIC ACID MONOHYDRATE; BISMUTH OXYCHLORIDE; MANDELIC ACID; .ALPHA.-TOCOPHEROL ACETATE; EDETATE DISODIUM ANHYDROUS; ETHYLHEXYL PALMITATE; PROPANEDIOL; GLUCONIC ACID; ADENOSINE; SODIUM BENZOATE; BUTYLATED HYDROXYTOLUENE; TETRADIUM RUTICARPUM FRUIT; SODIUM BICARBONATE; MAGNESIUM STEARATE; CAPRYLYL GLYCOL; ETHYLHEXYLGLYCERIN; HYALURONIC ACID; SILANETRIOL; HYALURONATE SODIUM; SORBIC ACID; HEXYLENE GLYCOL

Renewed Hope in a Jar spf 30

Drug Facts

Active Ingredients

Avobenzone (2.7%), Octinoxate (6.99%), Octocrylene (2%).

Purpose

Sunscreen

Uses

- helps prevent sunburn
- if used as directed with other sun protection measures (see Directions), decreases the risk of skin cancer and early skin aging caused by the sun

Warnings

- For external use only.

- Do not use on damaged or broken skin.

- When using this product keep out of eyes. Rinse with water to remove.

- Stop use and ask a doctor if rash occurs.

- Keep out of reach of children. If swallowed, get medical help or contact a Poison Control Center right away.

Directions

- apply to clean face in the morning. we recommend use with renewed hope in a jar eye
- apply liberally 15 minutes before sun exposure
- reapply at least every 2 hours
- use a water-resistant sunscreen if swimming or sweating
- Sun-Protection Measures: spending time in the sun increases your risk of skin cancer and early skin aging. to decrease this risk, regularly use a sunscreen with a broad spectrum spf value of 15 or higher and other Sun-Protection Measures including:
  - limit time in the sun, especially from 10 a.m. – 2 p.m.
  - wear long-sleeved shirts, pants, hats and sunglasses
  - children under 6 months: ask a doctor

Inactive Ingredients

water, carthamus tinctorius (safflower) oleosomes, butylene glycol, glycerin, c12-15 alkyl benzoate, methyl gluceth-20, glycolic acid, polyacrylamide, cyclopentasiloxane, ammonium acryloyldimethyltaurate/vp copolymer, hydrogenated lecithin, cyclohexasiloxane, phenoxyethanol, sodium hydroxide, c13-14 isoparaffin, cetyl alcohol, polysorbate 80, laureth-7, citric acid, fragrance, bismuth oxychloride, mandelic acid, tocopheryl acetate, disodium edta, synthetic fluorphlogopite, ethylhexyl palmitate, propanediol, gluconic acid, adenosine, sodium benzoate, bht, evodia rutaecarpa fruit extract, sodium bicarbonate, yeast extract, magnesium stearate, opuntia coccinellifera flower extract, silica dimethyl silylate, caprylyl glycol, ethylhexylglycerin, hyaluronic acid, silanetriol, sodium hyaluronate, sorbic acid, hexylene glycol.

Other Information

- protect this product from excessive heat and direct sun

Questions or Comments?

Call toll-free 1-800-568-3151 from 6 a.m. – 5 p.m. MST time (Monday – Friday)

Principal Display Panel - Renewed Hope in a Jar Carton Label

renewed
hope
in a jar spf 30

refreshing & refining moisturizer
broad spectrum spf 30 sunscreen

philosophy: live with optimism.

renew with hope.

60 ml/2 fl. oz,